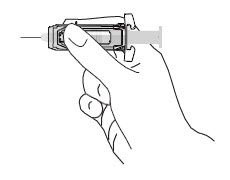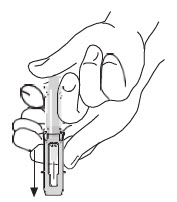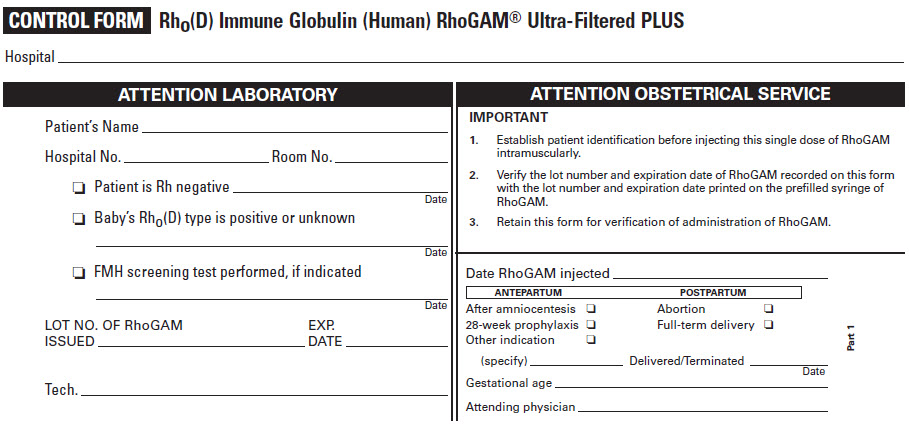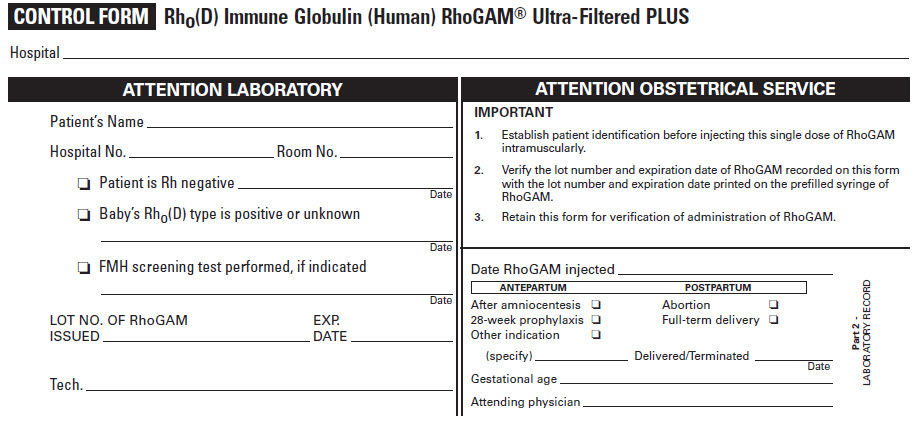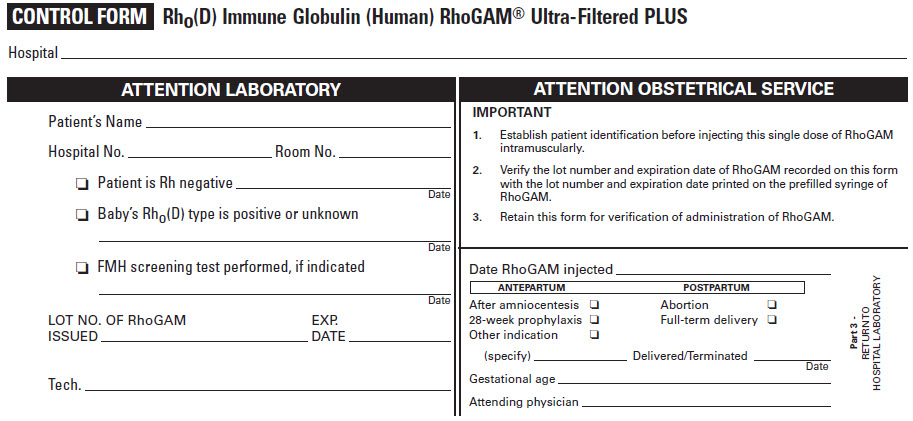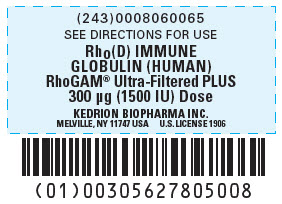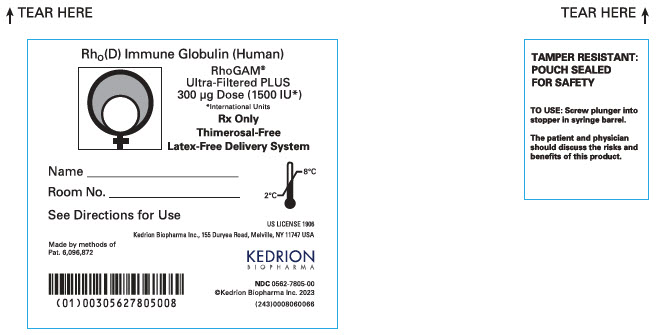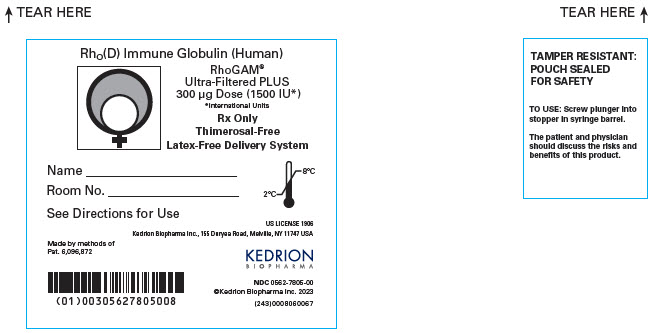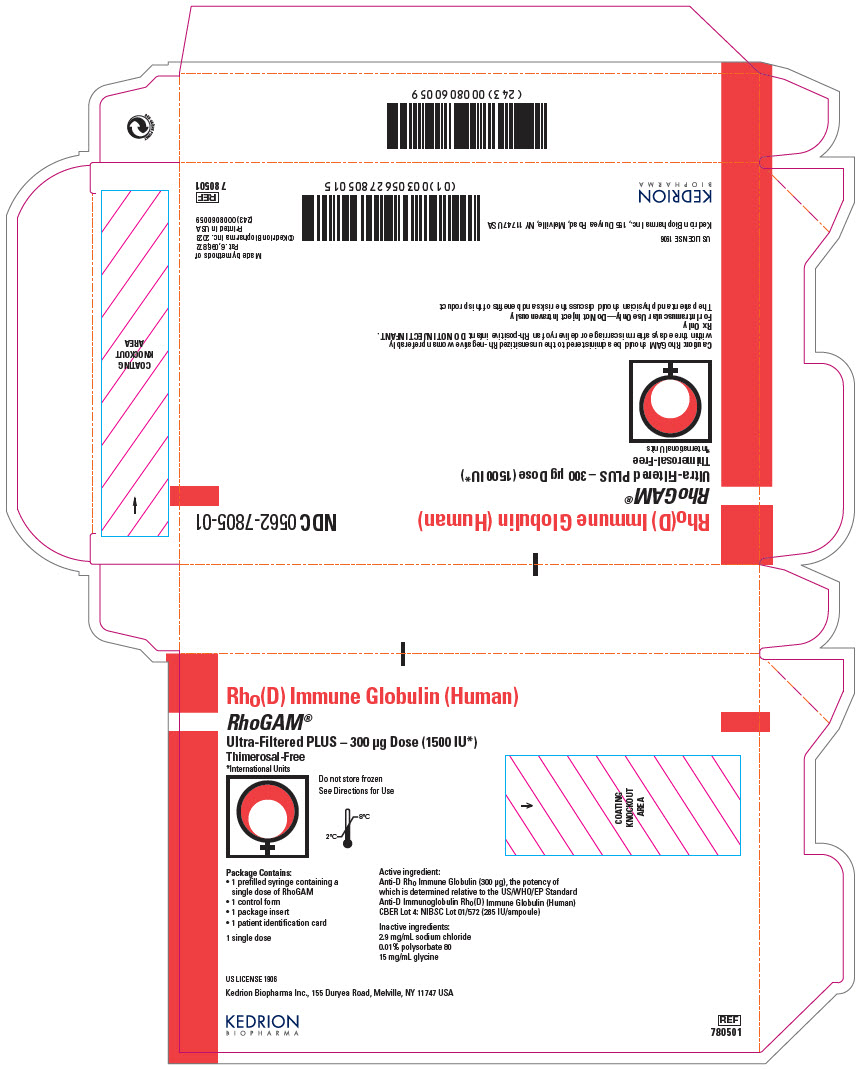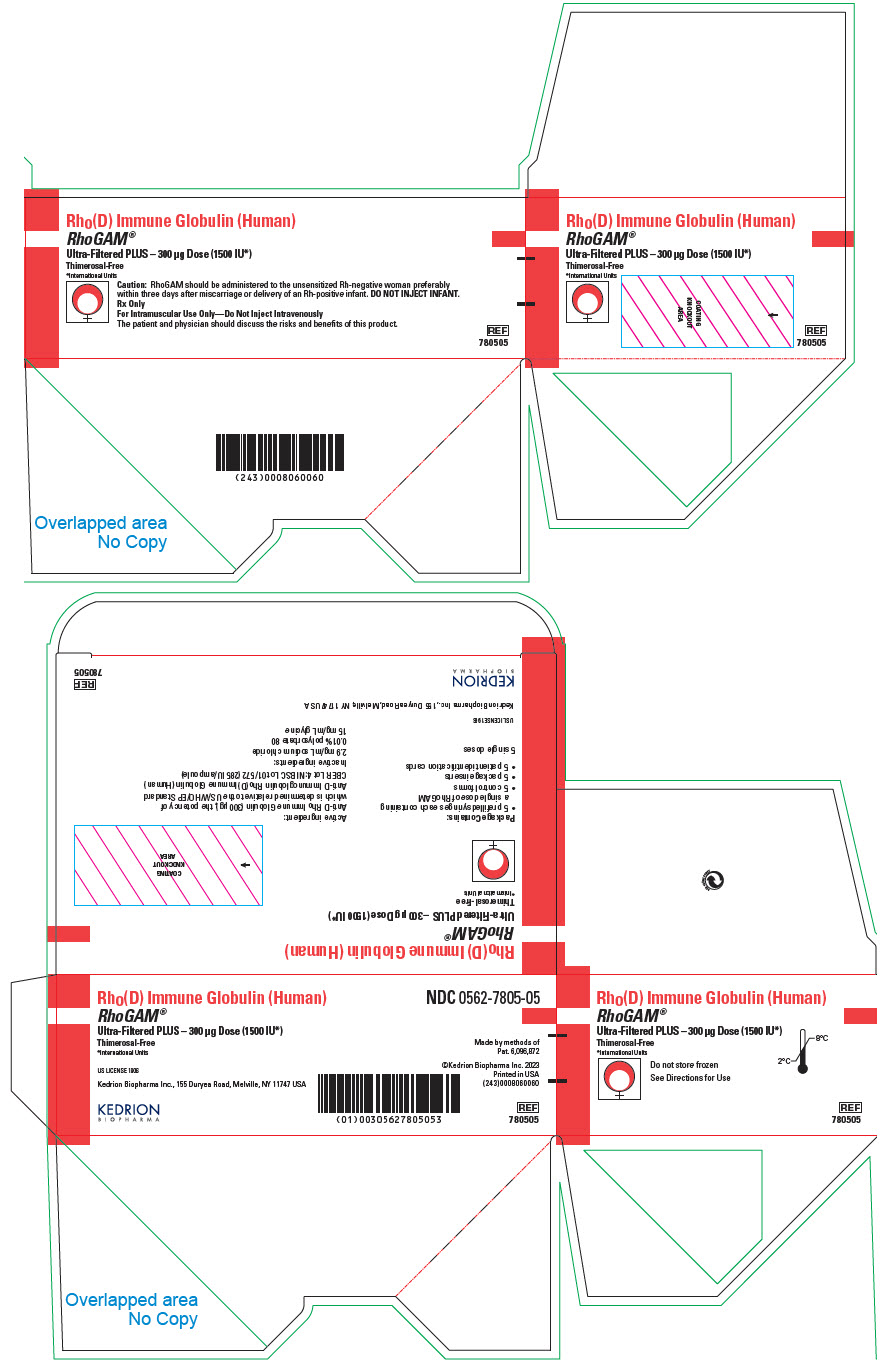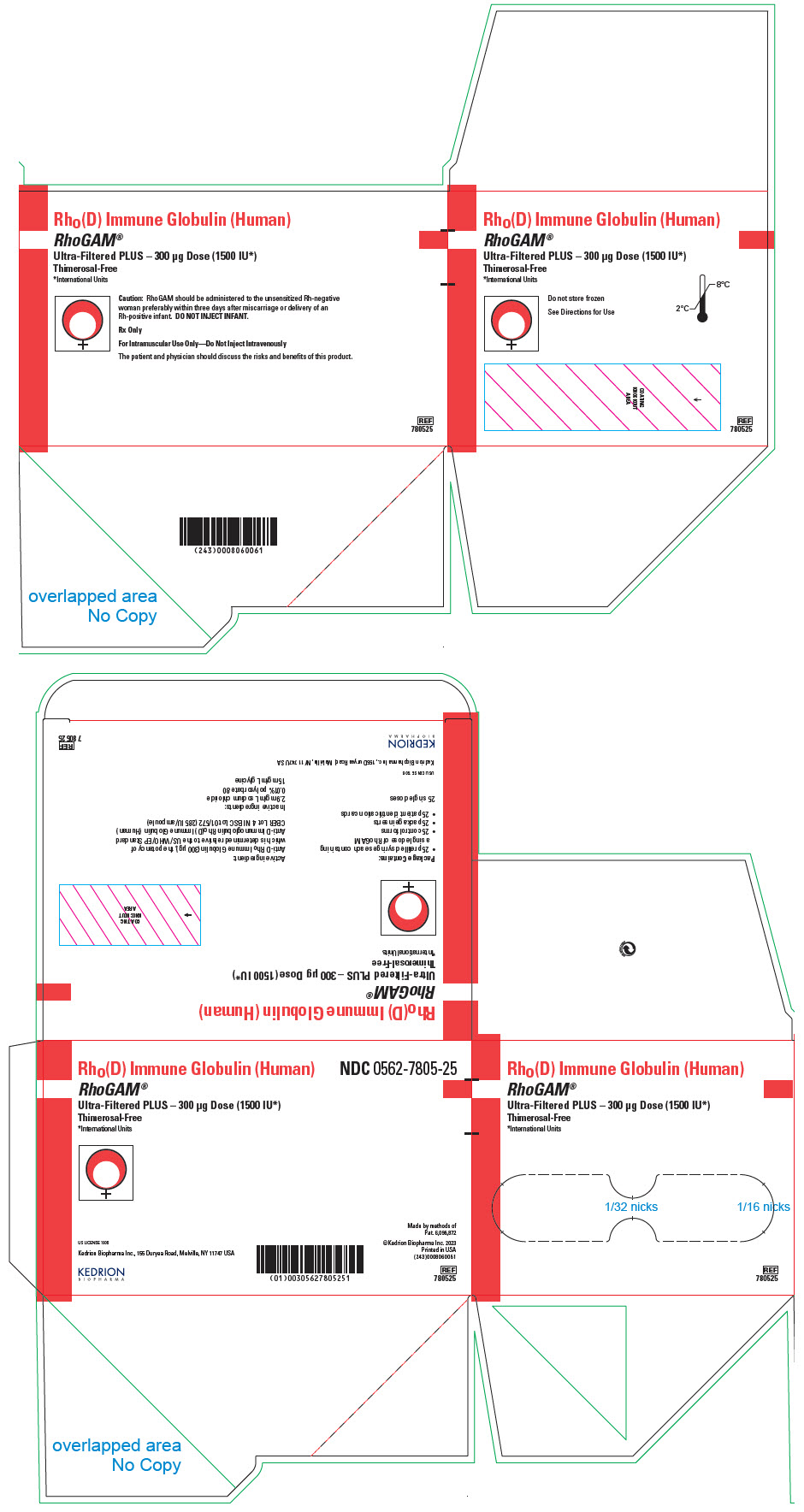 DRUG LABEL: RhoGAM Ultra-Filtered PLUS
NDC: 0562-7805 | Form: INJECTION, SOLUTION
Manufacturer: Kedrion Biopharma Inc
Category: other | Type: PLASMA DERIVATIVE
Date: 20250724

ACTIVE INGREDIENTS: HUMAN RHO(D) IMMUNE GLOBULIN 300 ug/1 1
INACTIVE INGREDIENTS: SODIUM CHLORIDE; GLYCINE; POLYSORBATE 80

HIGHLIGHTS OF PRESCRIBING INFORMATION

These highlights do not include all the information needed to use RhoGAM Ultra-Filtered PLUS (RhoGAM) safely and effectively. See full prescribing information for RhoGAM.
RhoGAM® Ultra-Filtered PLUS [Rho(D) Immune Globulin (Human)] (300 μg) (1500 IU), prefilled syringe, for intramuscular use
Initial U.S. Approval: 1968

RECENT MAJOR CHANGES

Description (11)

06/2025

1 INDICATIONS AND USAGE

RhoGAM is an immune globulin indicated for use in preventing Rh immunization for:

- Pregnancy and other obstetrical conditions in Rh-negative women unless the father or baby are conclusively Rh-negative, e.g. delivery of an Rh-positive baby irrespective of the ABO groups of the mother and baby, any antepartum fetal-maternal hemorrhage (suspected or proven), actual or threatened pregnancy loss at any stage of gestation and ectopic pregnancy. (1.1)
- Prevention of Rh immunization in any Rh-negative person after incompatible transfusion of Rh-positive blood or blood products. (1.2)
- Limitation of use
  Pregnancy and other obstetrical conditions: In the case of postpartum use, RhoGAM is intended for maternal administration. Do not inject the newborn infant. (1.3)

2 DOSAGE AND ADMINISTRATION

For intramuscular use only. (2)

Pregnancy and other obstetrical conditions (2.1)

Dose | Indication | Notes [After delivery, obstetric complications, and/or invasive procedures, the volume of the fetal-maternal hemorrhage must be determined to calculate the exact dose of RhoGAM required.]
RhoGAM (300 µg) (1500 IU) | Postpartum (if the newborn is Rh-positive) Administer within 72 hours of delivery | Additional doses of RhoGAM are indicated when the patient has been exposed to > 15 mL of Rh-positive red blood cells.
RhoGAM (300 µg) (1500 IU) | Antepartum:; - Prophylaxis at 26 to 28 weeks gestation Administer within 72 hours of suspected or proven exposure to Rh-positive red blood cells - Obstetric complications/ invasive procedures beyond 13 weeks gestation | If antepartum prophylaxis is indicated, it is essential that the mother receive a postpartum dose if the infant is Rh-positive.
RhoGAM (300 µg) (1500 IU) | Actual or threatened termination of pregnancy (spontaneous or induced) up to and including 12 weeks gestation Administer within 72 hours

Transfusion of Rh-incompatible blood or blood products (2.1)

Administer within 72 hours of suspected or proven exposure to Rh-positive red blood cells. (2.1)

Dose | Indication | Notes
RhoGAM (300 µg) (1500 IU) | ≥ 2.5 mL Rh-positive red blood cells | Administer 20 µg of RhoGAM per mL of Rh-positive red blood cell exposure, rounding up to the next whole syringe.

3 DOSAGE FORMS AND STRENGTHS

Rho(D) Immune Globulin (Human)

- RhoGAM® Ultra-Filtered PLUS - 300 μg (1500 IU) – Prefilled Syringes (3)

4 CONTRAINDICATIONS

- Rh-positive individuals. (4)
- Patients with a known history of anaphylactic or severe systemic reactions to the administration of human immune globulin products. (4)

5 WARNINGS AND PRECAUTIONS

- Severe hypersensitivity reactions may occur with the use of RhoGAM. (5.1)
- RhoGAM should be administered in a setting where appropriate equipment, medications such as epinephrine, and personnel trained in the management of hypersensitivity, anaphylaxis, and shock are available. (5.1)
- Products made from human blood may carry a risk of transmitting infectious agents e.g., viruses, the variant Creutzfeldt-Jakob disease (vCJD) and, theoretically, the Creutzfeldt-Jakob disease (CJD) agent. (5.2)
- After administration of Rho(D) immune globulin, a transitory increase of various passively transferred antibodies in the patient's blood may yield positive serological testing results. (5.3)

Incompatible blood transfusion

- Patients treated for Rh-incompatible transfusion should be monitored by clinical and laboratory means for signs and symptoms of a hemolytic reaction. (5.4)

6 ADVERSE REACTIONS

- The most frequently reported adverse reactions in patients receiving Rho(D) Immune Globulin (Human) products are injection site reactions, such as swelling, induration, redness and mild pain or warmth. Possible systemic reactions are skin rash, body aches or a slight elevation in temperature. (6)
- Severe systemic reactions include allergic reactions and hemolytic reactions. (6)

To report SUSPECTED ADVERSE REACTIONS, contact Kedrion Biopharma Inc. at 1-855-3KDRION (1-855-353-7466) or FDA at 1-800-FDA-1088 or www.fda.gov/medwatch. Outside of the United States, the company distributing these products should be contacted.

7 DRUG INTERACTIONS

- May impair the efficacy of live vaccines such as measles, mumps and varicella. Administration of live vaccines should generally be delayed until 12 weeks after the final dose of immune globulin. If administered within 14 days after administration of a live vaccine, the efficacy of the vaccination may be impaired. (7)
- The postpartum vaccination of rubella-susceptible women with rubella or MMR vaccine should not be delayed because of the receipt of Rho(D) Immune Globulin (Human). (7)

FULL PRESCRIBING INFORMATION

1 INDICATIONS AND USAGE

1.1 Pregnancy and other obstetrical conditions

RhoGAM is indicated for administration to Rh-negative women not previously sensitized to the Rho(D) factor, unless the father or baby are conclusively Rh-negative, in case of:

- Delivery of an Rh-positive baby irrespective of the ABO groups of the mother and baby
- Antepartum prophylaxis at 26 to 28 weeks gestation
- Antepartum fetal-maternal hemorrhage (suspected or proven) as a result of placenta previa, amniocentesis, chorionic villus sampling, percutaneous umbilical blood sampling, other obstetrical manipulative procedure (e.g., version) or abdominal trauma
- Actual or threatened pregnancy loss at any stage of gestation
- Ectopic pregnancy

1.2 Transfusion of Rh-incompatible blood or blood products

RhoGAM is indicated for prevention of Rh immunization in any Rh-negative person after incompatible transfusion of Rh-positive blood or blood products (e.g., red blood cells, platelet concentrates, granulocyte concentrates).

1.3 Limitation of use

Pregnancy and other obstetrical conditions

In the case of postpartum use, RhoGAM is intended for maternal administration. Do not inject the newborn infant.

2 DOSAGE AND ADMINISTRATION

For intramuscular use only.

2.1 Dose

Pregnancy and other obstetrical conditions

Dose | Indication | Notes [: After delivery, obstetric complications, and/or invasive procedures, the volume of the fetal-maternal hemorrhage must be determined to calculate the exact dose of RhoGAM required.]
RhoGAM (300 µg) (1500 IU) | Postpartum (if the newborn is Rh-positive) Administer within 72 hours of delivery. | Additional doses of RhoGAM are indicated when the patient has been exposed to > 15 mL of Rh-positive red blood cells. This may be determined by use of qualitative or quantitative tests for fetal-maternal hemorrhage.
RhoGAM (300 µg) (1500 IU) | Antepartum:; - Prophylaxis at 26 to 28 weeks gestation Administer within 72 hours of suspected or proven exposure to Rh-positive red blood cells resulting from: - Amniocentesis, chorionic villus sampling (CVS) and percutaneous umbilical blood sampling (PUBS) - Abdominal trauma or obstetrical manipulation - Ectopic pregnancy - Threatened pregnancy loss after 12 weeks gestation with continuation of pregnancy - Pregnancy termination (spontaneous or induced) beyond 12 weeks gestation | If antepartum prophylaxis is indicated, it is essential that the mother receive a postpartum dose if the infant is Rh-positive. If RhoGAM is administered early in pregnancy (before 26 to 28 weeks), there is an obligation to maintain a level of passively acquired anti-D by administration of RhoGAM at 12-week intervals.
RhoGAM (300 µg) (1500 IU) | Actual or threatened termination of pregnancy (spontaneous or induced) up to and including 12 weeks gestation Administer within 72 hours

- Administer RhoGAM every 12 weeks starting from first injection to maintain a level of passively acquired anti-D.
- If delivery occurs within three weeks after the last antepartum dose, the postpartum dose may be withheld, but a test for fetal-maternal hemorrhage should be performed to determine if exposure to > 15 mL of red blood cells has occurred.
- If delivery of the baby does not occur 12 weeks after the administration of the standard antepartum dose (at 26 to 28 weeks), a second dose is recommended to maximize protection antepartum.

RhoGAM dosage

Each single dose prefilled syringe of RhoGAM contains 300 μg (1500 IU) of Rho(D) Immune Globulin (Human). This is the dose for the indications associated with pregnancy at or beyond 13 weeks unless there is clinical or laboratory evidence of a fetal-maternal hemorrhage (FMH) in excess of 15 mL of Rh-positive red blood cells.

This dose will suppress the immune response to up to 2.5 mL of Rh-positive red blood cells. RhoGAM is indicated within 72 hours after termination of pregnancy up to and including 12 weeks gestation.

Multiple Dosage

Multiple doses of RhoGAM are required if a FMH exceeds 15 mL, an event that is possible but unlikely prior to the third trimester of pregnancy and is most likely at delivery. Patients known or suspected to be at increased risk of FMH should be tested for FMH by qualitative or quantitative methods.^3 In efficacy studies, RhoGAM was shown to suppress Rh immunization in all subjects when given at a dose of > 20 μg per mL of Rh-positive red blood cells. Thus, a single dose of RhoGAM will suppress the immune response after exposure to < 15 mL of Rh-positive red blood cells. However, in clinical practice, laboratory methods used to determine the amount of exposure (volume of transfusion or FMH) to Rh-positive red blood cells are imprecise. Therefore, administration of more than 20 μg of RhoGAM per mL of Rh-positive red blood cells should be considered whenever a large FMH or red blood cell exposure is suspected or documented. Multiple doses may be administered at the same time or at spaced intervals, as long as the total dose is administered within three days of exposure.^1

Transfusion of Rh-incompatible blood or blood products

Administer within 72 hours of suspected or proven exposure to Rh-positive red blood cells.

Dose | Indication | Notes
RhoGAM (300 µg) (1500 IU) | 2.5 - 15.0 mL Rh-positive red blood cells
RhoGAM (300 µg) (1500 IU) (multiple syringes) | > 15.0 mL Rh-positive red blood cells | Additional doses of RhoGAM are indicated when the patient has been exposed to > 15 mL of Rh-positive red blood cells. Administer 20 µg of RhoGAM per mL of Rh-positive red blood cell exposure, rounding up to the next whole syringe. Multiple doses may be administered at the same time or at spaced intervals, as long as the total dose is administered within three days of exposure.

2.2 Administration

- Visually inspect RhoGAM for particulate matter, discoloration and syringe damage prior to administration.
- Do not use if particulate matter is observed.
- RhoGAM is clear or slightly opalescent. Do not use if discolored.
- Administer injection per standard protocol.

Note: When administering RhoGAM intramuscularly, place fingers in contact with glass syringe barrel through windows in shield to prevent possible premature activation of safety guard.

After injection, to engage the safety guard, use free hand to slide safety guard over needle. An audible "click" indicates proper activation. Keep hands behind needle at all times. Dispose of the syringe in accordance with local regulations.

As with all blood products, patients should be observed for at least 20 minutes following administration of RhoGAM.

3 DOSAGE FORMS AND STRENGTHS

- RhoGAM® Ultra-Filtered PLUS - 300 μg (1500 IU) [The anti-D content of RhoGAM is expressed as μg per dose or as International Units (IU) per dose. The conversion factor is 1 μg = 5 IU.^2] – Prefilled Syringes

4 CONTRAINDICATIONS

The use of RhoGAM is contraindicated in the following:

- Rh-positive individuals
- Patients with a known history of anaphylactic or severe systemic reactions to the administration of human immune globulin products.

5 WARNINGS AND PRECAUTIONS

5.1 Hypersensitivity

Severe hypersensitivity reactions may occur with the use of RhoGAM, even in patients who have tolerated previous administrations.

RhoGAM contains a small quantity of IgA^3. There is a potential risk of hypersensitivity in IgA deficient individuals. Although high doses of intravenous immune globulin containing IgA at levels of 270-720 μg/mL have been given without incident during treatment of patients with high-titer antibodies to IgA^4, the attending physician must weigh the benefit against the potential risks of hypersensitivity reactions.

RhoGAM should be administered in a setting where appropriate equipment, medications such as epinephrine, and personnel trained in the management of hypersensitivity, anaphylaxis, and shock are available.

5.2 Transmissible Infectious Agents

Because RhoGAM is made from human blood, it may carry a risk of transmitting infectious agents, e.g., viruses, the variant Creutzfeldt-Jakob disease (vCJD) and, theoretically, the Creutzfeldt-Jakob disease (CJD) agent.

All infections thought by a physician possibly to have been transmitted by these products should be reported by the physician or other healthcare provider in the United States to Kedrion Biopharma Inc. at 1-855-3KDRION (1-855-353-7466). Outside the United States, the company distributing these products should be contacted. The physician should discuss the risks and benefits of these products with the patient.

5.3 Interference with Laboratory Tests

After administration of Rho(D) immune globulin, a transitory increase of various passively transferred antibodies in the patient's blood may yield positive serological testing results, with the potential for misleading interpretation. Passive transmission of antibodies to erythrocyte antigens (e.g., A, B, C and E) and other blood group antibodies may cause a positive direct or indirect antiglobulin (Coombs') test.

Recovery of anti-D in plasma or serum after injection of RhoGAM or other Rho(D) Immune Globulin (Human) products is highly variable among individuals. Anti-D detection in a patient's plasma is dependent on assay sensitivity and time of sample collection post-injection. Currently there are no requirements or practice standards to test for the presence of anti-D in order to determine adequacy or efficacy of dose following an injection of RhoGAM.

The presence of passively acquired anti-D antibodies in the maternal serum may cause a positive antibody screening test. This does not preclude further antepartum or postpartum prophylaxis.

A large fetomaternal hemorrhage late in pregnancy or following delivery may cause a weak mixed field positive Du test result. Assess such an individual for a large fetomaternal hemorrhage and adjust the dose of Rho(D) immune globulin accordingly. The presence of passively administered anti Rho(D) in maternal or fetal blood can lead to a positive direct antiglobulin (Coombs') test. If there is an uncertainty about the father's Rh group or immune status, administer Rho(D) immune globulin to the mother.

5.4 Hemolysis

Incompatible blood transfusion

Administration of RhoGAM to patients who are Rh-positive or have received Rh-positive red blood cells may result in signs and symptoms of a hemolytic reaction, including fever, back pain, nausea and vomiting, hypo- or hypertension, hemoglobinuria/emia, elevated bilirubin and creatinine and decreased haptoglobin. Therefore, patients treated for Rh-incompatible transfusion should be monitored by clinical and laboratory means for signs and symptoms of a hemolytic reaction. Alert patients to, and monitor them for, the signs and symptoms of intravascular hemolysis, including back pain, shaking chills, fever, and discolored urine or hematuria. Absence of these signs and/or symptoms of intravascular hemolysis within 8 hours do not indicate intravascular hemolysis cannot occur subsequently.

6 ADVERSE REACTIONS

The most frequently reported adverse reactions in patients receiving Rho(D) Immune Globulin (Human) products are injection site reactions, such as swelling, induration, redness and mild pain or warmth. Possible systemic reactions are skin rash, body aches or a slight elevation in temperature. Severe systemic reactions include allergic reactions and hemolytic reactions (see Warnings and Precautions [5.2]).

There have been no reported fatalities due to anaphylaxis or any other cause related to RhoGAM administration.

6.1 Clinical Studies Experience

Because clinical studies are conducted under different protocols and widely varying conditions, adverse reaction rates observed cannot be directly compared to rates in other clinical trials and may not reflect the rates observed in practice.

No clinical studies with RhoGAM have been conducted under the current Good Clinical Practices (GCP) Guidelines.

6.2 Postmarketing Experience

Because these reactions are reported voluntarily from a population of uncertain size, it is not always possible to reliably estimate their frequency or to establish a causal relationship to Rho(D) Immune Globulin (Human) products.

The following adverse reactions have been reported during post-approval use of RhoGAM: hypersensitivity reactions, including cases of anaphylactic shock or anaphylactoid reactions, skin rash, erythema, pruritus, chill, pyrexia, malaise, and back pain. Transient injection-site irritation and pain have been reported following intramuscular administration.

7 DRUG INTERACTIONS

7.1 Live Virus Vaccines

Immune globulin preparations including Rho(D) Immune Globulin (Human) may impair the efficacy of live vaccines such as measles, mumps and varicella. Administration of live vaccines should generally be delayed until 12 weeks after the final dose of immune globulin. If an immune globulin is administered within 14 days after administration of a live vaccine, the immune response to the vaccination may be inhibited.^5

Because of the importance of rubella immunity among women of childbearing age, the postpartum vaccination of rubella-susceptible women with rubella or MMR vaccine should not be delayed because of the receipt of Rho(D) Immune Globulin (Human) during the last trimester of pregnancy or at delivery. Vaccination should occur immediately after delivery and if possible, testing should be performed after 3 or more months to ensure immunity to rubella and if necessary, to measles.^5

8 USE IN SPECIFIC POPULATIONS

8.1 Pregnancy

Risk Summary

RhoGAM is used in pregnant women for the suppression or Rh isoimmunization. The available evidence suggests that Rho(D) Immune Globulin (Human) does not harm the fetus or affect future pregnancies or reproduction capacity when given to pregnant Rh0(D)-negative women for suppression of Rh isoimmunization.^6

Animal reproduction studies have not been conducted with RhoGAM.

8.2 Lactation

Risk Summary

RhoGAM can be used during breastfeeding. Immunoglobulins are excreted in human milk.

8.4 Pediatric Use

Safety and effectiveness in pediatric patients have not been established.

8.5 Geriatric Use

No clinical studies have been performed in geriatric subjects.

10 OVERDOSAGE

There are no reports of known overdoses in patients being treated with RhoGAM.

11 DESCRIPTION

RhoGAM Rho(D) Immune Globulin (Human) is a sterile solution containing immunoglobulin G (IgG) anti-D (anti-Rh) for use in preventing Rh immunization. It is manufactured from human plasma containing anti-D from Rh-negative donors immunized with Rh-positive red blood cells. A single dose of RhoGAM contains sufficient anti-D (300 μg or 1500 IU) to suppress the immune response to up to 15 mL of Rh-positive red blood cells.^7 The anti-D dose is measured by comparison to the RhoGAM in-house reference standard, the potency of which is established relative to the U.S./World Health Organization/European Pharmacopoeia Standard Anti-D Immunoglobulin Rho(D) Immune Globulin (Human).^8

Plasma for RhoGAM is typically sourced from a donor center owned and operated by KEDPlasma LLC., US Lic. No. 1876. All donors are carefully screened by history and laboratory testing to reduce the risk of transmitting blood-borne pathogens from infected donors. Each plasma donation is tested and found to be non-reactive for the presence of hepatitis B surface antigen (HBsAg) and antibodies to hepatitis C (HCV) and human immunodeficiency viruses (HIV) 1 and 2. Additionally, plasma is tested by FDA licensed Nucleic Acid Testing (NAT) for hepatitis B virus (HBV), HCV and HIV-1. Each plasma unit must be negative (non-reactive) in all tests. Plasma is tested by in-process NAT procedures for hepatitis A virus (HAV) and parvovirus B19 (B19) in a minipool format. Only plasma that has passed virus screening is used for production. The NAT procedure for B19 detects all three genotypes based upon sequence alignment of known virus isolates. The limit of B19 DNA in the manufacturing pool is set not to exceed 10^4 IU per mL.

Fractionation of the plasma is performed by a modification of the cold alcohol procedure that has been shown to significantly lower viral titers.^3 Following plasma fractionation, a viral clearance filtration step and a viral inactivation step are performed. The viral filtration step removes both enveloped and non‐enveloped viruses as small as approximately 20 nm via a size-exclusion mechanism.

Following viral filtration, quality control tests are performed on the 20 nm filtration membrane to ensure filter integrity. The viral inactivation step (Solvent/Detergent treatment) utilizes Triton X-100 and tri-n-butyl phosphate (TNBP) to inactivate enveloped viruses such as HCV, HIV, HBV and West Nile Virus (WNV).^(3,9, 10, 11)

The donor selection process, the fractionation process, the viral filtration step, the viral inactivation process and other manufacturing process steps increase product safety by reducing the virus load potentially present in the starting material and thus reducing the risk of transmission of enveloped and non-enveloped viruses. Rho(D) Immune Globulin (Human) intended for intramuscular use and prepared by cold alcohol fractionation has not been shown to transmit hepatitis or other infectious diseases.^12 There have been no documented cases of infectious disease transmission by RhoGAM.

Laboratory spiking studies, performed in accordance with good laboratory practices ^3 have shown that the cumulative viral removal and inactivation capability of the RhoGAM manufacturing process is as follows:

Virus | HIV-1 | BVDV | PRV | PPV | EMCV
Lipid Enveloped | Yes | Yes | Yes | No | No
Size (nm) | 80-120 | 40-70 | 120-200 | 18-24 | 25-30
Genome | ss-RNA | ss-RNA | ds-DNA | ss-DNA | ss-RNA
Step
Methanol precipitation | 5.16 | 4.46 | 4.95 | 4.02 | 4.57
Depth filtration | ≥ 4.95 | 2.53 | 2.34 | 3.83 | Not Significant (<1 Log)
Viral Grade Filtration (Nanofiltration) | > 3.64 (> 5.13) [The lower reduction factor value (corresponding to the removal mechanism only) was used for the calculation of the Total Viral Reduction(log10), instead of the total reduction value which derives from both removal and inactivation mechanisms (value in brackets).] | >2.93 (> 5.31) | > 6.02 | 4.52 | > 4.61
Solvent/Detergent treatment | ≥ 5.08 | ≥ 4.47 | ≥ 4.05 | N/A | N/A
Total Viral Reduction | ≥ 18.83 | ≥ 14.39 | ≥ 17.36 | 12.37 | > 9.18
Units = log10 reduction
HIV Human Immunodeficiency Virus, Relevant virus for HIV-1 and 2 and model virus for Human T-cell Lymphotropic Virus (HTLV) 1 and 2
BVDV Bovine Viral Diarrhea Virus, Model for Hepatitis C Virus and West Nile Virus (WNV)
PRV Pseudorabies Virus, Model for large, enveloped DNA viruses such as Herpes Viruses and Hepatitis B Virus
PPV Porcine Parvovirus, Model for Parvovirus B19
EMCV Encephalomyocarditis Virus, Model for Hepatitis A Virus
N/A Not Applicable

The safety of Rho(D) Immune Globulin (Human) has been further shown in an empirical study of viral marker rates in female blood donors in the United States.^13 This study revealed that Rh-negative donors, of whom an estimated 55-60% had received Rho(D) Immune Globulin (Human) for pregnancy-related indications, had prevalence and incidence viral marker rates similar to those of Rh-positive female donors who had not received Rho(D) Immune Globulin (Human).

The final product contains 5 ± 1% IgG, 2.9 mg/mL sodium chloride, 0.01% Polysorbate 80 (non-animal derived) and 15 mg/mL glycine. Small amounts of IgA, typically less than 15 μg per dose, are present.^3 The pH range is 6.20 - 7.00 and IgG purity is > 98%. The product contains no added human serum albumin (HSA), no thimerosal or other preservatives and utilizes a latex-free delivery system.

RhoGAM Ultra-Filtered PLUS is manufactured by Kedrion Biopharma Inc., 155 Duryea Road, Melville, NY 11747 USA.

12 CLINICAL PHARMACOLOGY

12.1 Mechanism of Action

RhoGAM acts by suppressing the immune response of Rh-negative individuals to Rh-positive red blood cells. The mechanism of action is unknown. RhoGAM and other Rho(D) Immune Globulin (Human) products are not effective in altering the course or consequences of Rh immunization once it has occurred.

12.2 Pharmacodynamics

Use after Rh-Incompatible Transfusion

An Rh-negative individual transfused with one unit of Rh-positive red blood cells has about an 80% likelihood of producing anti-D. However, Rh immunization can occur after exposure to < 1 mL of Rh-positive red blood cells. Protection from Rh immunization is accomplished by administering > 20 μg of RhoGAM per mL of Rh-positive red blood cells within 72 hours of transfusion of incompatible red blood cells.^14,15,16

12.3 Pharmacokinetics

Pharmacokinetic studies after intramuscular injection were performed on sixteen Rh-negative subjects receiving a single dose of (368 μg or 1840 IU) RhoGAM.^3 Plasma anti-D levels were monitored for thirteen weeks using a validated Automated Quantitative Hemagglutination method with sensitivity of approximately 1 ng/mL. The following mean pharmacokinetic parameters were obtained from data collected over the first ten weeks of a thirteen-week study:

Parameter | Mean | SD | Units
Maximum plasma concentration obtained (Cmax) | 54.0 | 13.0 | ng/mL
Time to attain Cmax (Tmax) | 4 |  | days
Elimination half-life (T1/2) | 30.9 | 13.8 | days
Volume of distribution (Vd) | 7.3 | 1.5 | liters
Clearance (CL) | 150.4 | 53.3 | mL/day

14 CLINICAL STUDIES

Rho(D) Immune Globulin (Human) administered at 28 weeks, as well as within 72 hours of delivery, has been shown to reduce the Rh immunization rate to about 0.1-0.2%.^15,16 Clinical studies demonstrated that administration of Rh immune globulin within three hours following pregnancy termination was 100% effective in preventing Rh immunization.^17

Multiple studies have been performed that prove the safety and efficacy of RhoGAM in both the obstetrical and post transfusion settings.

Pollack, Gorman and colleagues^18 studied the efficacy of RhoGAM in the postpartum setting in a randomized, controlled study completed in 1967. The control group received no immunoglobulin therapy after delivery, while the test group received 300 μg of RhoGAM intramuscularly within 72 hours of delivery of an Rh-positive infant. Six months after delivery, the incidence of Rh immunization in the control group was 6.4% (32/499) versus 0.13% (1/781) in the RhoGAM group (p < 0.001).

Pollack et al. performed two randomized, placebo-controlled studies in the post transfusion setting that were designed to establish the dose response relationship of RhoGAM. In the first study,^7 178 (176 males, 2 females) Rh-negative volunteers received varying volumes of Rh- positive red cells; 92 subjects then received RhoGAM. A single dose of RhoGAM (1.1 mL @ 267 μg/mL) was shown to suppress anti-D formation after injection of up to 15.1 mL of Rh-positive red cells. In a companion study, Pollack administered 500 mL of Rh-positive whole blood to 44 Rh-negative male volunteers. Twenty-two (22) subjects received 20 μg RhoGAM per mL of Rh-positive red cells and 22 received no RhoGAM. None of the RhoGAM-treated subjects developed anti-D; 18/22 control arm subjects developed anti-D (p < 0.0001) ^19.

A study was conducted in 1985 using the low protein formulation of RhoGAM. None of the 30 Rh negative male volunteers who received RhoGAM after injection of 15 ml of Rh positive red cells developed anti-D.

15 REFERENCES

1 AABB Technical Manual. 19th ed. Bethesda, Maryland: AABB, October 2017.
2 Gunson HH, Bowell PJ, Kirkwood TBL. Collaborative study to recalibrate the International Reference Preparation of anti-D immunoglobulin. J Clin Pathol 1980;33:249-53.
3 Data on file at Kedrion Biopharma Inc.
4 Cunningham-Rundles C, Zhuo Z, Mankarious S, Courter S. Long-term use of IgA- depleted intravenous immunoglobulin in immunodeficient subjects with anti-IgA antibodies. J Clin Immunol 1993;13:272-78.
5 Centers for Disease Control and Prevention. General recommendations on immunization: recommendations of the Advisory Committee on Immunization Practices and the American Academy of Family Physicians. MMWR 2002;51 (No. RR-2):6-7.
6 Thornton JG, Page C, Foote G, Arthur GR, Tovey LAD, Scott JS. Efficacy and long term effects of antenatal propylaxis with anti-D immunoglobulin. Br Med J. 1989;298: 1671-1673
7 Pollack W, Ascari WQ, Kochesky RJ, O'Connor RR, Ho TY, Tripodi D. Studies on Rh prophylaxis. I. Relationship between doses of anti-Rh and size of antigenic stimulus. Transfusion 1971;11:333-39.
8 Thorpe SJ, Sands D, Fox B, Behr‐Gross ME, Schaffner G, Yu MW. A global standard for anti‐D immunoglobulin: international collaborative study to evaluate a candidate preparation. Vox Sang 2003;85:313‐21.
9 Roth, NJ et al. Nanofiltration as a robust method contributing to viral safety of plasma‐derived therapeutics: 20 years' experience of the plasma protein manufacturers. Transfusion 2020 Nov; 60(11):2661‐2674
10 Horowitz B, Wiebe ME, Lippin A, Stryker MH. Inactivation of viruses in labile blood derivatives. I. Disruption of lipid-enveloped viruses by tri (n-butyl) phosphate detergent combinations. Transfusion 1985; 25(6):516-22.
11 Dichtelmüller HO et al. Robustness of solvent/detergent treatment of plasma derivatives: a data collection from Plasma Protein Therapeutics Association member companies. Transfusion. 2009 Sep;49(9):1931‐43.
12. Tabor E. The epidemiology of virus transmission by plasma derivatives: clinical studies verifying the lack of transmission of hepatitis B and C viruses and HIV type 1. Transfusion 1999;39:1160-68.
13 Watanabe KK, Busch MP, Schreiber GB, Zuck TF. Evaluation of the safety of Rh Immunoglobulin by monitoring viral markers among Rh-negative female blood donors. Vox Sang 2000;8:1-6.
14 Zipursky A, Israels LG. The pathogenesis and prevention of Rh immunization. Can Med Assoc J 1967;97:1245-56.
15 de Haas M, Finning K, Massey E, Roberts DJ. Anti-D prophylaxis: past, present and future. Transfus Med 2014;24:1–7. (ex 22-24)
16 Bowman J. Thirty-five years of Rh prophylaxis. Transfusion 2003;43:1661–6. (ex 22-24)
17 Stewart FH, Burnhill MS, Bozorgi N. Reduced dose of Rh immunoglobulin following first trimester pregnancy termination. Obstet Gynecol 1978;51:318-22.
18 Pollack, W., Gorman, J.G., Freda, V.J., Ascari, W.Q., Allen, A.E. and Baker, W.J. (1968), Results of Clinical Trials of RhoGAM in Women. Transfusion, 8: 151-153.
19 Pollack W, Ascari WQ, Crispen JF, O'Connor RR, Ho TY. Studies on Rh prophylaxis. II. Rh immune prophylaxis after transfusion with Rh-positive blood. Transfusion. 1971 Nov-Dec;11(6):340-4.

16 HOW SUPPLIED / STORAGE AND HANDLING

The following presentations of RhoGAM are available:

Presentation | Product description/ package sizes | Carton NDC number | Primary container NDC number
RhoGAM® Ultra-Filtered PLUS (300 µg) (1500 IU) – Carton of 1 syringe | 1 prefilled single-dose syringe in a pouch, 1 package insert, 1 control form, 1 patient identification card | NDC 0562-7805-01 | prefilled single-dose syringe NDC 0562-7805-00
RhoGAM® Ultra-Filtered PLUS (300 µg) (1500 IU) – Carton of 5 syringes | 5 prefilled single-dose syringe in a pouch, 5 package insert, 5 control form, 5 patient identification card | NDC 0562-7805-05 | prefilled single-dose syringe NDC 0562-7805-00
RhoGAM® Ultra-Filtered PLUS (300 µg) (1500 IU) – Carton of 25 syringes | 25 prefilled single-dose syringe in a pouch, 25 package insert, 25 control form, 25 patient identification card | NDC 0562-7805-25 | prefilled single-dose syringe NDC 0562-7805-00

STORAGE AND HANDLING

Store at 2 to 8°C. Do not store frozen.

Do not use after the expiration date printed on the syringe.

17 PATIENT COUNSELING INFORMATION

Please inform patients of the following:

- The risks and benefits of RhoGAM.
- The most common adverse reactions are local reactions including swelling, induration, redness and mild pain at the site of injection, and a small number of patients have noted a slight elevation in temperature.
- Allergic reactions to RhoGAM may occur. Patients should be observed for at least 20 minutes after administration. Signs of hypersensitivity reactions include hives, generalized urticaria, tightness of the chest, wheezing, hypotension and anaphylaxis.
- RhoGAM may interfere with the response to live virus vaccines (e.g., measles, mumps, rubella, and varicella). Instruct patients to notify their healthcare professional of this potential interaction when they are receiving vaccinations.
- RhoGAM is prepared from human plasma and may contain infectious agents that can cause disease. Numerous tests have been applied in the plasma collection process and specific viral inactivation steps have been added to the manufacturing process to minimize the risk of transmission of diseases, but all risk cannot be eliminated.
- Retain the RhoGAM Patient Identification Card and advise the patient to retain the card and present it to other health care providers when appropriate.

SUMMARY OF REVISIONS
The PI was amended to update the nanofilter used for manufacturing and eliminate Ortho Clinical Diagnostics, Inc as a manufacturer. As a result, all information related to Viresolve filter has been replaced with nanofilter, the viral clearance table revised, and Ortho Clinical Diagnostics, Inc has been deleted. The technical-scientific information related to nanofilter, has been revised from the following section: Description (11)

US LICENSE 1906
Kedrion Biopharma Inc., 155 Duryea Road, Melville, NY 11747 USA

©Kedrion Biopharma Inc. 2024
Printed in U.S.A.
Made by methods of
U.S. Pat. 6,096,872
U.S. Pat. 7,655,233

(243)0008060072

PATIENT IDENTIFICATION CARD

Name

Address

I AM Rh NEGATIVE. I have received a protective injection of RhoGAM® Rho(D) Immune Globulin (Human) Ultra-Filtered PLUS. IMPORTANT: Anti-Rh antibody (also called anti-D) will be present in my blood for several weeks after the injection, and may be detectable by laboratory testing. The presence of this passive anti-Rh antibody does not disqualify me from receiving additional injections of RhoGAM as indicated and prescribed by my physician.

© Kedrion Biopharma Inc. 2024

Rho(D) Immune Globulin (Human)

RhoGAM®
Ultra-Filtered PLUS

This 3-part form contains:

- Directions for Use
- Patient Control Form
- Patient Identification Card

US LICENSE 1906
Kedrion Biopharma Inc., 155 Duryea Road, Melville, NY 11747 USA

(243)0008060072

Date of Injection of RhoGAM

(circle product administered)

Lot No.

Exp. Date

Injection was:

❏ at pregnancy termination

❏ during pregnancy

❏ after delivery

Attending Physician

Physician's Telephone Number

PRINCIPAL DISPLAY PANEL - 300 μg Syringe Label

(243)0008060065

SEE DIRECTIONS FOR USE

Rho(D) IMMUNE
GLOBULIN (HUMAN)
RhoGAM® Ultra-Filtered PLUS
300 μg (1500 IU) Dose

KEDRION BIOPHARMA INC.
MELVILLE, NY 11747 USA
U.S. LICENSE 1906

PRINCIPAL DISPLAY PANEL - 300 μg Syringe Pouch Label

↑ TEAR HERE

Rho(D) Immune Globulin (Human)

RhoGAM®
Ultra-Filtered PLUS
300 μg Dose (1500 IU*)
*International Units

Rx Only

Thimerosal-Free

Latex-Free Delivery System

Name ______________________
Room No. ___________________

See Directions for Use

US LICENSE 1906

Kedrion Biopharma Inc., 155 Duryea Road, Melville, NY 11747 USA

Made by methods of
Pat. 6,096,872

KEDRION
BIOPHARMA

NDC 0562-7805-00
©Kedrion Biopharma Inc. 2023
(243)0008060066

TEAR HERE ↑

TAMPER RESISTANT:
POUCH SEALED
FOR SAFETY

TO USE: Screw plunger into
stopper in syringe barrel.

The patient and physician
should discuss the risks and
benefits of this product.

PRINCIPAL DISPLAY PANEL - 300 μg Syringe Pouch Label (Rework)

↑ TEAR HERE

Rho(D) Immune Globulin (Human)

RhoGAM®
Ultra-Filtered PLUS
300 μg Dose (1500 IU*)
*International Units

Rx Only

Thimerosal-Free

Latex-Free Delivery System

Name ______________________
Room No. ___________________

See Directions for Use

US LICENSE 1906

Kedrion Biopharma Inc., 155 Duryea Road, Melville, NY 11747 USA

Made by methods of
Pat. 6,096,872

KEDRION
BIOPHARMA

NDC 0562-7805-00
©Kedrion Biopharma Inc. 2023
(243)0008060067

TEAR HERE ↑

TAMPER RESISTANT:
POUCH SEALED
FOR SAFETY

TO USE: Screw plunger into
stopper in syringe barrel.

The patient and physician
should discuss the risks and
benefits of this product.

PRINCIPAL DISPLAY PANEL - 300 μg Syringe Pouch Carton - 01

Rho(D) Immune Globulin (Human)
RhoGAM®
Ultra-Filtered PLUS – 300 μg Dose (1500 IU*)
Thimerosal-Free
*International Units

Do not store frozen

See Directions for Use

Package Contains:

- 1 prefilled syringe containing a
  single dose of RhoGAM
- 1 control form
- 1 package insert
- 1 patient identification card

1 single dose

Active ingredient:
Anti-D Rho Immune Globulin (300 μg), the potency of
which is determined relative to the US/WHO/EP Standard
Anti-D Immunoglobulin Rho(D) Immune Globulin (Human)
CBER Lot 4: NIBSC Lot 01/572 (285 IU/ampoule)

Inactive ingredients:
2.9 mg/mL sodium chloride
0.01% polysorbate 80
15 mg/mL glycine

US LICENSE 1906

Kedrion Biopharma Inc., 155 Duryea Road, Melville, NY 11747 USA

KEDRION
BIOPHARMA

REF
780501

PRINCIPAL DISPLAY PANEL - 300 μg Syringe Pouch Carton - 05

Rho(D) Immune Globulin (Human)
RhoGAM®
Ultra-Filtered PLUS – 300 μg Dose (1500 IU*)
Thimerosal-Free
*International Units

Caution: RhoGAM should be administered to the unsensitized Rh-negative woman preferably
within three days after miscarriage or delivery of an Rh-positive infant. DO NOT INJECT INFANT.

Rx Only

For Intramuscular Use Only—Do Not Inject Intravenously

The patient and physician should discuss the risks and benefits of this product.

REF
780505

PRINCIPAL DISPLAY PANEL - 300 μg Syringe Pouch Carton - 25

Rho(D) Immune Globulin (Human)
RhoGAM®
Ultra-Filtered PLUS – 300 μg Dose (1500 IU*)
Thimerosal-Free
*International Units

Caution: RhoGAM should be administered to the unsensitized Rh-negative
woman preferably within three days after miscarriage or delivery of an
Rh-positive infant. DO NOT INJECT INFANT.

Rx Only

For Intramuscular Use Only—Do Not Inject Intravenously

The patient and physician should discuss the risks and benefits of this product.

REF
780525